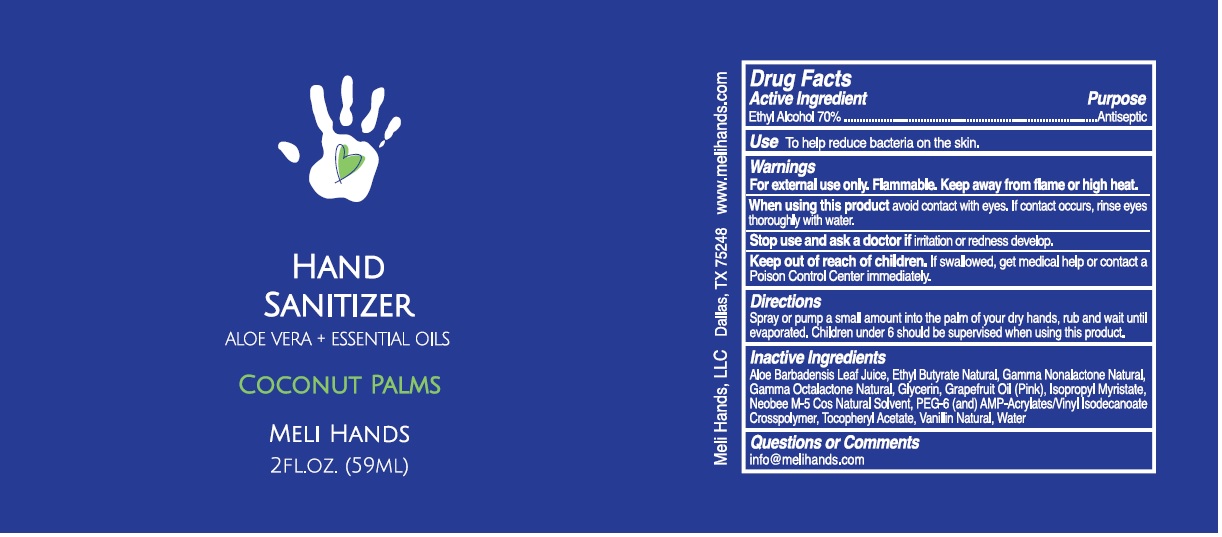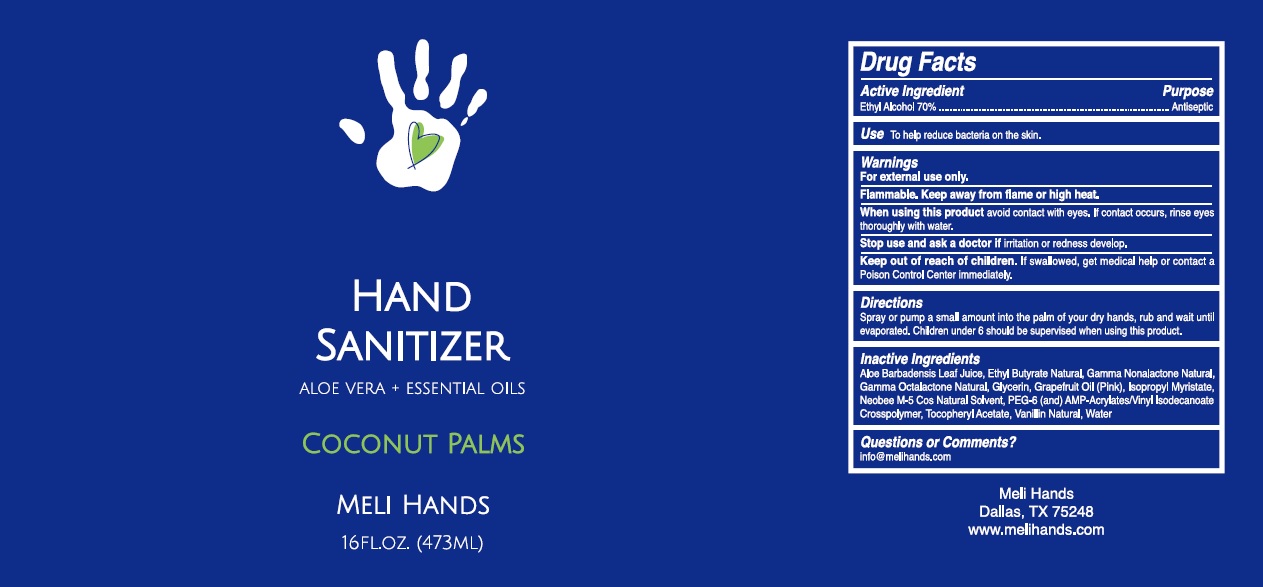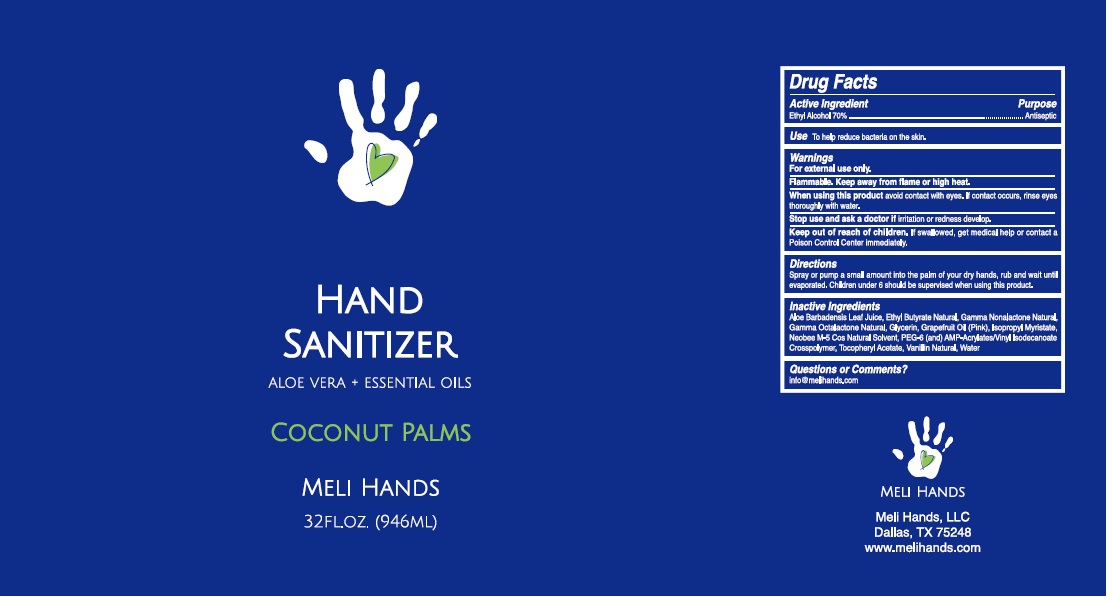 DRUG LABEL: MELI HANDS HAND SANITIZER
NDC: 79426-103 | Form: LIQUID
Manufacturer: MELI HANDS, LLC
Category: otc | Type: HUMAN OTC DRUG LABEL
Date: 20211216

ACTIVE INGREDIENTS: ALCOHOL 70 mL/100 mL
INACTIVE INGREDIENTS: ALOE VERA LEAF; ETHYL BUTYRATE; .GAMMA.-NONALACTONE; .GAMMA.-OCTALACTONE; GLYCERIN; GRAPEFRUIT OIL; ISOPROPYL MYRISTATE; MEDIUM-CHAIN TRIGLYCERIDES; POLYETHYLENE GLYCOL 300; AMINOMETHYLPROPANOL; ACRYLATES/VINYL ISODECANOATE CROSSPOLYMER (10000 MPA.S NEUTRALIZED AT 0.5%); .ALPHA.-TOCOPHEROL ACETATE; VANILLIN; WATER

MELI HANDS HAND SANITIZER COCONUT PALMS

Active Ingredient

Ethyl Alcohol 70%

Purpose

Antiseptic

Use

To help reduce bacteria on the skin.

Warnings

For external use only. Flammable. Keep away from flame or high heat.

When using this product avoid contact with eyes. If contact occurs, rinse eyes thoroughly with water.

Stop use and ask a doctor if irritation or redness develop.

Keep out of reach of children. If swallowed, get medical help or contact a Poison Control Center immediately.

Directions

Spray or pump a small amount into the palm of your dry hands, rub and wait until evaporated. Children under 6 should be supervised when using this product.

Inactive Ingredients

Aloe Barbadensis Leaf Juice, Ethyl Butyrate Natural, Gamma Nonalactone Natural, Gamma Octalactone Natural, Glycerin, Grapefruit Oil (Pink), Isopropyl Myristate, Neobee M-5 Cos Natural Solvent, PEG-6 (and) AMP-Acrylates/Vinyl Isodecanoate Crosspolymer, Tocopheryl Acetate, Vanillin Natural, Water

Questions or Comments?

info@melihands.com

ALOE VERA + ESSENTIAL OILS

COCONUT PALMS

Meli Hands, LLC

Dallas, TX 75248

www.melihands.com